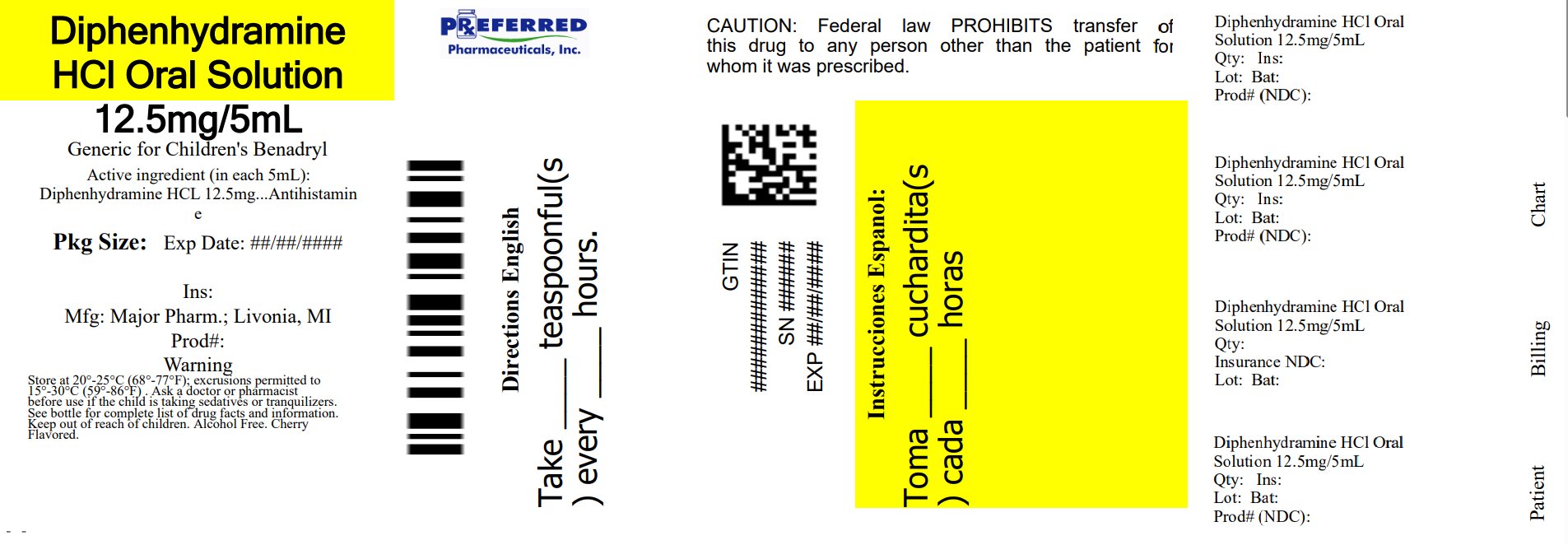 DRUG LABEL: Diphenhydramine HCl
NDC: 68788-8274 | Form: SOLUTION
Manufacturer: Preferred Pharmaceuticals Inc.
Category: otc | Type: HUMAN OTC DRUG LABEL
Date: 20250328

ACTIVE INGREDIENTS: DIPHENHYDRAMINE HYDROCHLORIDE 12.5 mg/5 mL
INACTIVE INGREDIENTS: ANHYDROUS CITRIC ACID; D&C RED NO. 33; FD&C RED NO. 40; GLYCERIN; HIGH FRUCTOSE CORN SYRUP; WATER; SODIUM BENZOATE; SODIUM CHLORIDE; TRISODIUM CITRATE DIHYDRATE; SUCROSE

Major 44-015-DSP

Active ingredient (in each teaspoonful (5 mL))

Diphenhydramine HCl 12.5 mg

Purpose

Antihistamine

Uses

- temporarily relieves these symptoms due to hay fever or other upper respiratory allergies:
  - runny nose
  - sneezing
  - itchy, watery eyes
  - itching of the nose or throat

Warnings

Do not use

- to make a child sleepy
- with any other product containing diphenhydramine, even one used on skin

Ask a doctor before use if you have

- a breathing problem such as emphysema or chronic bronchitis
- glaucoma
- difficulty in urination due to enlargement of the prostate gland

Ask a doctor or pharmacist before use if you are

taking sedatives or tranquilizers.

When using this product

- avoid alcoholic beverages
- alcohol, sedatives, and tranquilizers may increase drowsiness
- excitability may occur, especially in children
- marked drowsiness may occur
- use caution when driving a motor vehicle or operating machinery

If pregnant or breast-feeding,

ask a health professional before use.

Keep out of reach of children.

In case of overdose, get medical help or contact a Poison Control Center right away.

Directions

- do not take more than 6 doses in 24 hours
- mL = milliliter; FL OZ = fluid ounce
- find right dose on chart below
- take every 4 to 6 hours, or as directed by a doctor

Age | Dose
adults and children 12 years and over | 2 - 4 teaspoonsful (25 mg to 50 mg)
children 6 to 11 years | 1 - 2 teaspoonsful (12.5 mg to 25 mg)
children 2 to 5 years | do not use unless directed by a doctor
children under 2 years | do not use

Other information

- each teaspoonful (5 mL) contains: sodium 5 mg
- store at 25°C (77°F); excursions permitted between 15°-30°C (59°-86°F)
- use by expiration date on package

Inactive ingredients

anhydrous citric acid, D&C red #33, FD&C red #40, flavors, glycerin, high fructose corn syrup, purified water, sodium benzoate, sodium chloride, sodium citrate dihydrate, sucrose

Questions or comments?

(800) 616-2471

Relabeled By: Preferred Pharmaceuticals Inc.

Principal display panel

MAJOR®

NDC 68788-8274-1

Relabeled By: Preferred Pharmaceuticals Inc.

Diphenhydramine HCl
Oral Solution

Antihistamine

12.5 mg/5 mL

Institutional Dispensing only

Cherry Flavored
Alcohol Free

TAMPER EVIDENT: DO NOT USE IF IMPRINTED SAFETY SEAL UNDER CAP IS BROKEN OR MISSING

50844 REV1019A01521
Distributed by: MAJOR® PHARMACEUTICALS
Livonia, MI 48152
Rev. 03/21 M-17

Relabeled By: Preferred Pharmaceuticals Inc.